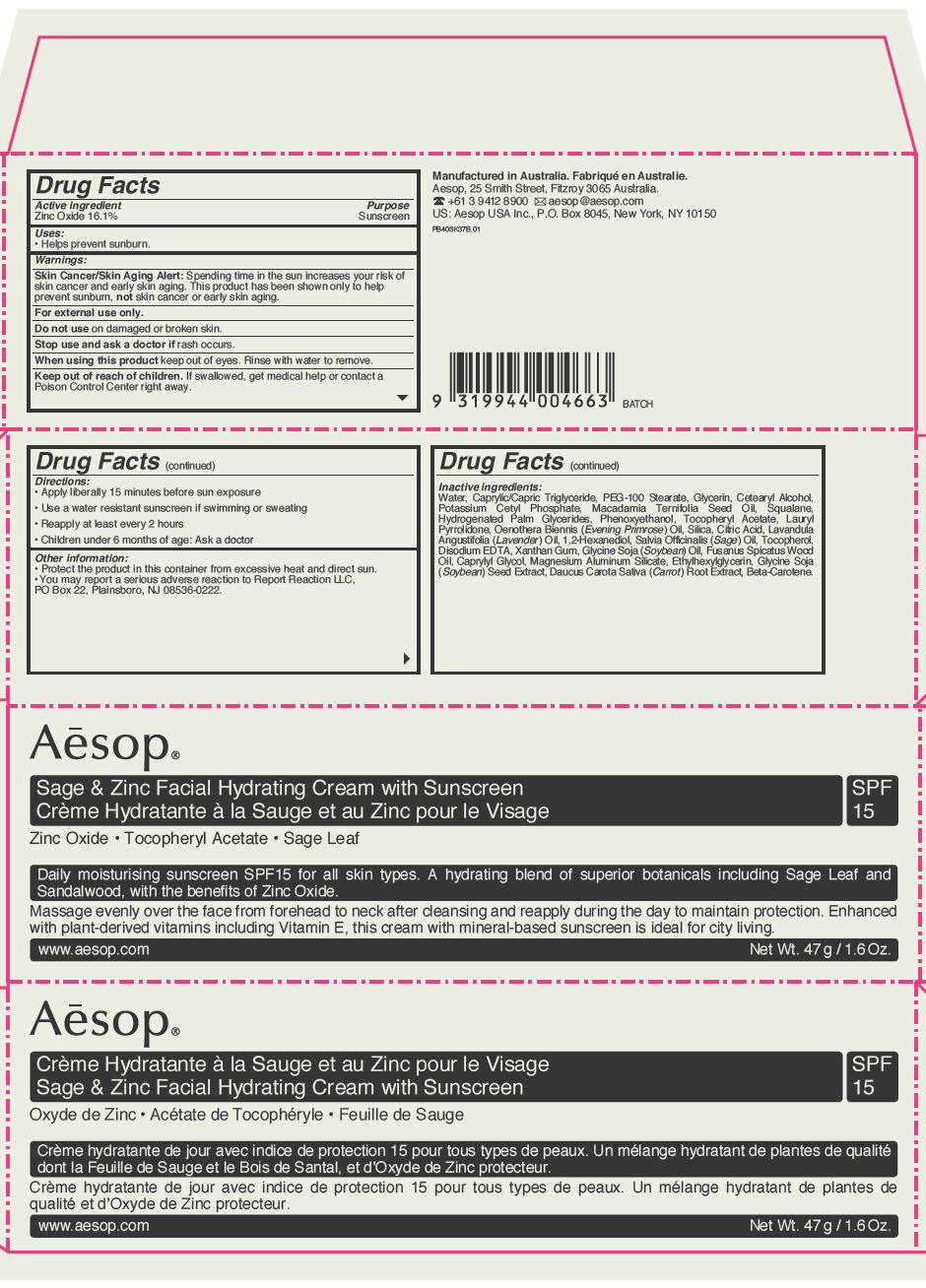 DRUG LABEL: Sage And Zinc Facial Hydrating
NDC: 76293-037 | Form: CREAM
Manufacturer: Emeis Cosmetics Pty Ltd
Category: otc | Type: HUMAN OTC DRUG LABEL
Date: 20111117

ACTIVE INGREDIENTS: Zinc Oxide 0.26 g/1.54 g
INACTIVE INGREDIENTS: Medium-Chain Triglycerides; Water; PEG-100 Stearate; Glycerin; Cetostearyl Alcohol; Potassium Cetyl Phosphate; Macadamia Oil; Squalane; Hydrogenated Palm Glycerides; Phenoxyethanol; .Alpha.-Tocopherol Acetate, DL-; Lauryl Pyrrolidone; Evening Primrose Oil; Silicon Dioxide; Citric Acid Monohydrate; Lavender Oil; 1,2-Hexanediol; Sage Oil; Tocopherol; Edetate Disodium; Xanthan Gum; Soybean Oil; Santalum Spicatum Oil; Caprylyl Glycol; Magnesium Aluminum Silicate; Ethylhexylglycerin; Soybean; Carrot; Beta Carotene

Aēsop®
Sage & Zinc Facial Hydrating Cream with Sunscreen

Drug Facts

Active ingredient

Zinc Oxide 16.1%

Purpose

Sunscreen

Uses

- Helps prevent sunburn.

Warnings

Skin Cancer/Skin Aging Alert

Spending time in the sun increases your risk of skin cancer and early skin aging. This product has been shown only to help prevent sunburn, not skin cancer or early skin aging.

WHEN USING

For external use only.

Do not use on damaged or broken skin.

Stop use and ask a doctor if rash occurs.

When using this product keep out of eyes. Rinse with water to remove.

Keep out of reach of children. If swallowed, get medical help or contact a Poison Control Center right away.

Directions

- Apply liberally 15 minutes before sun exposure
- Use a water resistant sunscreen if swimming or sweating
- Reapply at least every 2 hours
- Children under 6 months of age: Ask a doctor

Other information

- Protect the product in this container from excessive heat and direct sun.
- You may report a serious adverse reaction to Report Reaction LLC, PO Box 22, Plainsboro, NJ 08536-0222.

Inactive ingredients

Water, Caprylic/Capric Triglyceride, PEG-100 Stearate, Glycerin, Cetearyl Alcohol, Potassium Cetyl Phosphate, Macadamia Ternifolia Seed Oil, Squalane, Hydrogenated Palm Glycerides, Phenoxyethanol, Tocopheryl Acetate, Lauryl Pyrrolidone, Oenothera Biennis (Evening Primrose) Oil, Silica, Citric Acid, Lavandula Angustifolia (Lavender) Oil, 1,2-Hexanediol, Salvia Officinalis (Sage) Oil, Tocopherol, Disodium EDTA, Xanthan Gum, Glycine Soja (Soybean) Oil, Fusanus Spicatus Wood Oil, Caprylyl Glycol, Magnesium Aluminum Silicate, Ethylhexylglycerin, Glycine Soja (Soybean) Seed Extract, Daucus Carota Sativa (Carrot) Root Extract, Beta-Carotene.

Manufactured in Australia.
Aesop, 25 Smith Street, Fitzroy 3065 Australia.

PRINCIPAL DISPLAY PANEL - 47 g Tube Carton

Aēsop®

Sage & Zinc Facial Hydrating Cream with Sunscreen
SPF
15

Zinc Oxide • Tocopheryl Acetate • Sage Leaf

Daily moisturising sunscreen SPF15 for all skin types. A hydrating blend of superior botanicals including Sage Leaf and
Sandalwood, with the benefits of Zinc Oxide.

Massage evenly over the face from forehead to neck after cleansing and reapply during the day to maintain protection. Enhanced
with plant-derived vitamins including Vitamin E, this cream with mineral-based sunscreen is ideal for city living.

www.aesop.com
Net Wt. 47 g / 1.6 Oz.